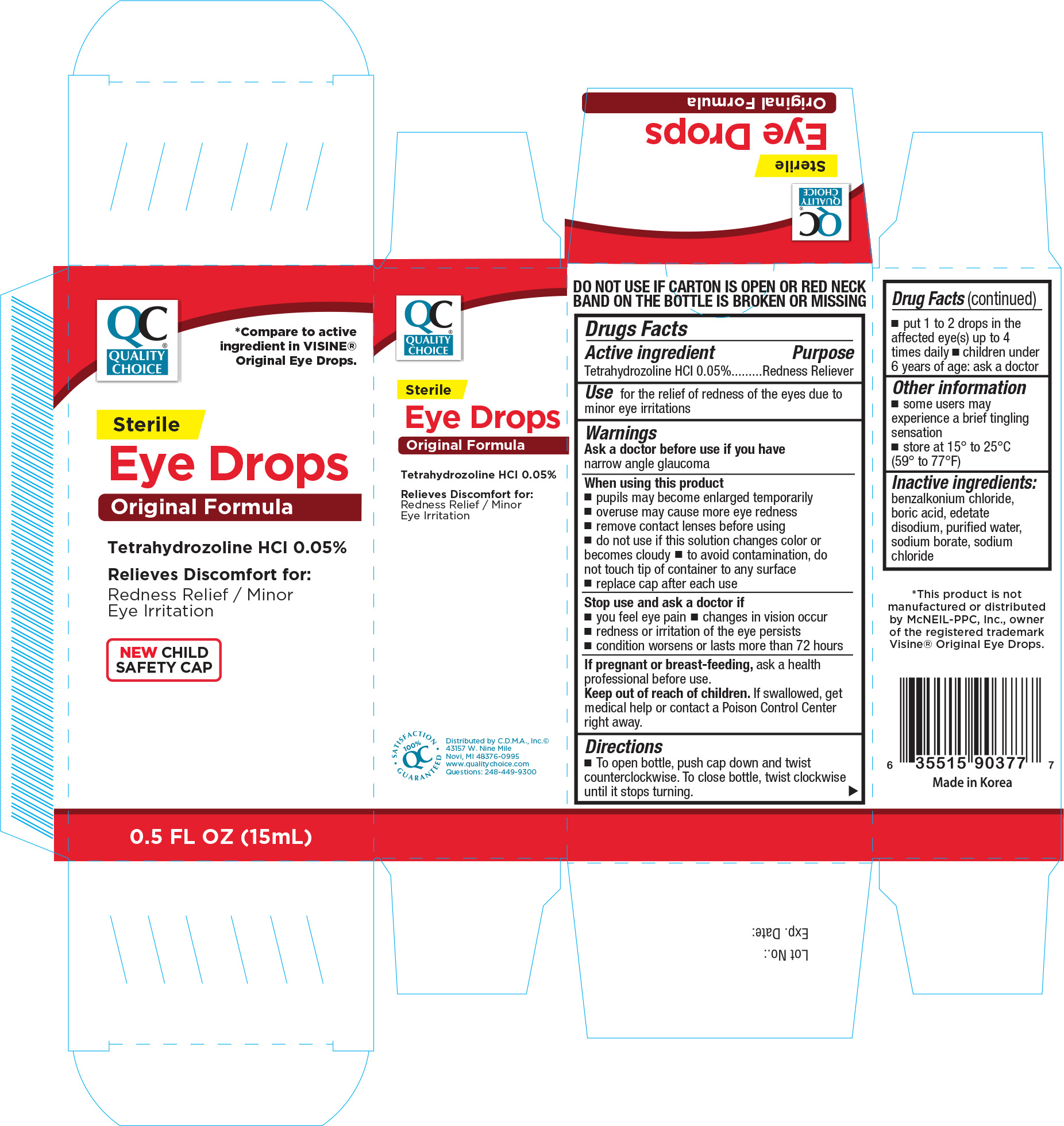 DRUG LABEL: QUALITY CHOICE ORIGINAL EYE DROPS
NDC: 63868-903 | Form: SOLUTION
Manufacturer: CHAIN DRUG MARKETING ASSOCIATION INC
Category: otc | Type: HUMAN OTC DRUG LABEL
Date: 20170322

ACTIVE INGREDIENTS: TETRAHYDROZOLINE HYDROCHLORIDE 0.5 mg/1 mL
INACTIVE INGREDIENTS: BENZALKONIUM CHLORIDE; BORIC ACID; EDETATE DISODIUM; SODIUM CHLORIDE; SODIUM BORATE; WATER

Active ingredient Purpose

Tetrahydrozoline HCL 0.05%.........................................Redness reliever

Uses

- for the relief of redness of the eyes due to minor eye irritations

Warnings

Ask a doctor before use if you have narrow angle glaucoma

When using this product

- pupils may become enlarged temporarily
- overuse may cause more eye redness
- remove contact lenses before using
- do not use if this solution changes color or becomes cloudy
- to avoid contamination, do not touch tip of container to any surface
- replace cap after each use

Stop use and ask a doctor if

- you feel eye pain
- changes in vision occur
- redness or irritation of the eye lasts
- condition worsens or lasts more than 72 hours

PREGNANCY OR BREAST FEEDING

If pregnant or breast-feeding, ask a health professional before use.

Keep out of reach of children.

If swallowed, get medical help or contact a Poison Control Center right away.

Directions

- to open bottle, push cap down and twist counterclockwise. To close bottle, twist clockwise until it stops turning
- put 1 to 2 drops in the affected eye(s) up to 4 times daily
- children under 6 years of age: ask a doctor

Other information

- some users may experience a brief tingling sensation
- store at 15o to 25oC (59o to 77oF)

INACTIVE INGREDIENT

Inactive ingredients: benzalkonium chloride, boric acid, edetate disodium, purified water, sodium chloride, and sodium borate

DOSAGE AND ADMINISTRATION

Distributed by

C.D.M.A., Inc.

43157 W. Nine Mile

Novi, MI 48376-0995

www.qualitychoice.com

Made in Korea